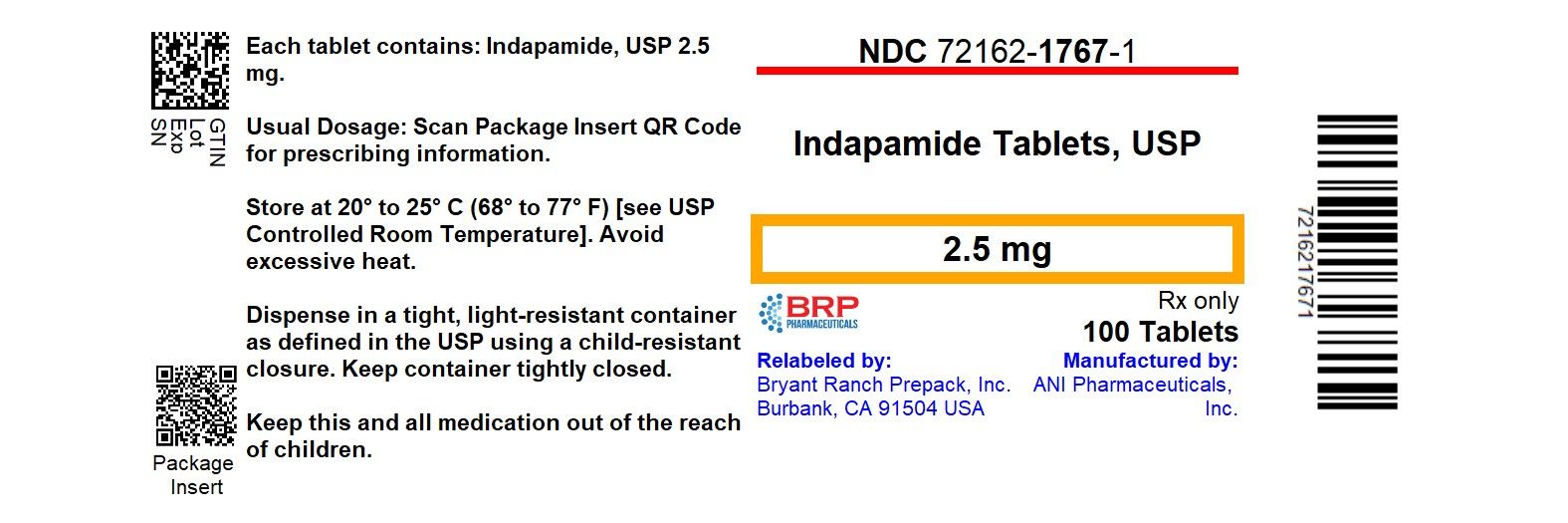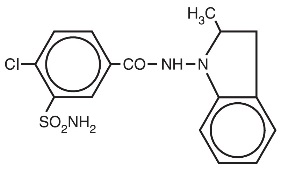 DRUG LABEL: Indapamide
NDC: 72162-1767 | Form: TABLET, FILM COATED
Manufacturer: Bryant Ranch Prepack
Category: prescription | Type: HUMAN PRESCRIPTION DRUG LABEL
Date: 20260226

ACTIVE INGREDIENTS: INDAPAMIDE 2.5 mg/1 1
INACTIVE INGREDIENTS: STARCH, CORN; HYPROMELLOSE, UNSPECIFIED; LACTOSE MONOHYDRATE; MAGNESIUM STEARATE; MICROCRYSTALLINE CELLULOSE; POLYETHYLENE GLYCOL, UNSPECIFIED; POLYSORBATE 80; TALC; TITANIUM DIOXIDE

Indapamide Tablets USP
Rx only

DESCRIPTION

Indapamide is an oral antihypertensive/diuretic. Its molecule contains both a polar sulfamoyl chlorobenzamide moiety and a lipid-soluble methylindoline moiety. It differs chemically from the thiazides in that it does not possess the thiazide ring system and contains only one sulfonamide group. The chemical name of indapamide is 4-Chloro- N-(2-methyl-1-indolinyl)-3-sulfamoylbenzamide, and its molecular weight is 365.84. The compound is a weak acid, pKa=8.8, and is soluble in aqueous solutions of strong bases. It is a white to yellow-white crystalline (tetragonal) powder.

Each tablet, for oral administration, contains 1.25 mg or 2.5 mg of indapamide USP and the following inactive ingredients: corn starch, hypromellose, lactose monohydrate, magnesium stearate, microcrystalline cellulose, polyethylene glycol, polysorbate 80, talc, and titanium dioxide. Additionally, the 1.25 mg product contains FD&C yellow #6 aluminum lake.

CLINICAL PHARMACOLOGY

Indapamide is the first of a new class of antihypertensive/diuretics, the indolines. The oral administration of 2.5 mg (two 1.25 mg tablets) of indapamide to male subjects produced peak concentrations of approximately 115 ng/mL of the drug in the blood within 2 hours. The oral administration of 5 mg (two 2.5 mg tablets) of indapamide to healthy male subjects produced peak concentrations of approximately 260 ng/mL of the drug in the blood within 2 hours. A minimum of 70% of a single oral dose is eliminated by the kidneys and an additional 23% by the gastrointestinal tract, probably including the biliary route. The half-life of indapamide in whole blood is approximately 14 hours.

Indapamide is preferentially and reversibly taken up by the erythrocytes in the peripheral blood. The whole blood/plasma ratio is approximately 6:1 at the time of peak concentration and decreases to 3.5:1 at 8 hours. From 71% to 79% of the indapamide in plasma is reversibly bound to plasma proteins.

Indapamide is an extensively metabolized drug, with only about 7% of the total dose administered, recovered in the urine as unchanged drug during the first 48 hours after administration. The urinary elimination of^14C-labeled indapamide and metabolites is biphasic with a terminal half-life of excretion of total radioactivity of 26 hours.

In a parallel design double-blind, placebo controlled trial in hypertension, daily doses of indapamide between 1.25 mg and 10 mg produced dose-related antihypertensive effects. Doses of 5 mg and 10 mg were not distinguishable from each other although each was differentiated from placebo and 1.25 mg indapamide. At daily doses of 1.25 mg, 5 mg and 10 mg, a mean decrease of serum potassium of 0.28, 0.61 and 0.76 mEq/L, respectively, was observed and uric acid increased by about 0.69 mg/100 mL.

In other parallel design, dose-ranging clinical trials in hypertension and edema, daily doses of indapamide between 0.5 mg and 5 mg produced dose related effects. Generally, doses of 2.5 mg and 5 mg were not distinguishable from each other although each was differentiated from placebo and from 0.5 mg or 1 mg indapamide. At daily doses of 2.5 mg and 5 mg a mean decrease of serum potassium of 0.5 and 0.6 mEq/Liter, respectively, was observed and uric acid increased by about 1 mg/100 mL.

At these doses, the effects of indapamide on blood pressure and edema are approximately equal to those obtained with conventional doses of other antihypertensive/diuretics.

In hypertensive patients, daily doses of 1.25 mg, 2.5 mg and 5 mg of indapamide have no appreciable cardiac inotropic or chronotropic effect. The drug decreases peripheral resistance with little or no effect on cardiac output, rate or rhythm. Chronic administration of indapamide to hypertensive patients has little or no effect on glomerular filtration rate or renal plasma flow.

Indapamide had an antihypertensive effect in patients with varying degrees of renal impairment, although in general, diuretic effects declined as renal function decreased.

In a small number of controlled studies, indapamide taken with other antihypertensive drugs such as hydralazine, propranolol, guanethidine, and methyldopa, appeared to have the additive effect typical of thiazide-type diuretics.

INDICATIONS AND USAGE

Indapamide tablets are indicated for the treatment of hypertension, alone or in combination with other antihypertensive drugs.

Indapamide tablets are also indicated for the treatment of salt and fluid retention associated with congestive heart failure.

Usage in Pregnancy

The routine use of diuretics in an otherwise healthy woman is inappropriate and exposes mother and fetus to unnecessary hazard (see PRECAUTIONS).

Diuretics do not prevent development of toxemia of pregnancy, and there is no satisfactory evidence that they are useful in the treatment of developed toxemia.

Edema during pregnancy may arise from pathological causes or from the physiologic and mechanical consequences of pregnancy. Indapamide is indicated in pregnancy when edema is due to pathologic causes, just as it is in the absence of pregnancy (however, see PRECAUTIONS). Dependent edema in pregnancy, resulting from restriction of venous return by the expanded uterus, is properly treated through elevation of the lower extremities and use of support hose; use of diuretics to lower intravascular volume in this case is illogical and unnecessary. There is hypervolemia during normal pregnancy which is not harmful to either the fetus or the mother (in the absence of cardiovascular disease), but which is associated with edema, including generalized edema in the majority of pregnant women. If this edema produces discomfort, increased recumbency will often provide relief. In rare instances, this edema may cause extreme discomfort which is not relieved by rest. In these cases, a short course of diuretics may provide relief and may be appropriate.

CONTRAINDICATIONS

Anuria.

Known hypersensitivity to indapamide or to other sulfonamide-derived drugs.

WARNINGS

Severe cases of hyponatremia, accompanied by hypokalemia have been reported with recommended doses of indapamide. This occurred primarily in elderly females. (See PRECAUTIONS, Geriatric Use.) This appears to be dose related. Also, a large case-controlled pharmacoepidemiology study indicates that there is an increased risk of hyponatremia with indapamide 2.5 mg and 5 mg doses. Hyponatremia considered possibly clinically significant (< 125 mEq/L) has not been observed in clinical trials with the 1.25 mg dosage (see PRECAUTIONS). Thus, patients should be started at the 1.25 mg dose and maintained at the lowest possible dose. (See DOSAGE AND ADMINISTRATION.)

Hypokalemia occurs commonly with diuretics (see ADVERSE REACTIONS, Hypokalemia), and electrolyte monitoring is essential, particularly in patients who would be at increased risk from hypokalemia, such as those with cardiac arrhythmias or who are receiving concomitant cardiac glycosides.

In general, diuretics should not be given concomitantly with lithium because they reduce its renal clearance and add a high risk of lithium toxicity. Read prescribing information for lithium preparations before use of such concomitant therapy.

PRECAUTIONS

General

Hypokalemia, Hyponatremia, and Other Fluid and Electrolyte Imbalances

Periodic determinations of serum electrolytes should be performed at appropriate intervals. In addition, patients should be observed for clinical signs of fluid or electrolyte imbalance, such as hyponatremia, hypochloremic alkalosis, or hypokalemia. Warning signs include dry mouth, thirst, weakness, fatigue, lethargy, drowsiness, restlessness, muscle pains or cramps, hypotension, oliguria, tachycardia, and gastrointestinal disturbance. Electrolyte determinations are particularly important in patients who are vomiting excessively or receiving parenteral fluids, in patients subject to electrolyte imbalance (including those with heart failure, kidney disease, and cirrhosis), and in patients on a salt-restricted diet.

The risk of hypokalemia secondary to diuresis and natriuresis is increased when larger doses are used, when the diuresis is brisk, when severe cirrhosis is present, and during concomitant use of corticosteroids or ACTH. Interference with adequate oral intake of electrolytes will also contribute to hypokalemia. Hypokalemia can sensitize or exaggerate the response of the heart to the toxic effects of digitalis, such as increased ventricular irritability.

Dilutional hyponatremia may occur in edematous patients; the appropriate treatment is restriction of water rather than administration of salt, except in rare instances when the hyponatremia is life threatening. However, in actual salt depletion, appropriate replacement is the treatment of choice. Any chloride deficit that may occur during treatment is generally mild and usually does not require specific treatment except in extraordinary circumstances as in liver or renal disease. Thiazide-like diuretics have been shown to increase the urinary excretion of magnesium; this may result in hypomagnesemia.

Hyperuricemia and Gout

Serum concentrations of uric acid increased by an average of 0.69 mg/100 mL in patients treated with indapamide 1.25 mg, and by an average of 1 mg/100 mL in patients treated with indapamide 2.5 mg and 5 mg, and frank gout may be precipitated in certain patients receiving indapamide (see ADVERSE REACTIONS). Serum concentrations of uric acid should, therefore, be monitored periodically during treatment.

Renal Impairment

Indapamide, like the thiazides, should be used with caution in patients with severe renal disease, as reduced plasma volume may exacerbate or precipitate azotemia. If progressive renal impairment is observed in a patient receiving indapamide, withholding or discontinuing diuretic therapy should be considered. Renal function tests should be performed periodically during treatment with indapamide.

Impaired Hepatic Function

Indapamide, like the thiazides, should be used with caution in patients with impaired hepatic function or progressive liver disease, since minor alterations of fluid and electrolyte balance may precipitate hepatic coma.

Glucose Tolerance

Latent diabetes may become manifest and insulin requirements in diabetic patients may be altered during thiazide administration. A mean increase in glucose of 6.47 mg/dL was observed in patients treated with indapamide 1.25 mg, which was not considered clinically significant in these trials. Serum concentrations of glucose should be monitored routinely during treatment with indapamide.

Calcium Excretion

Calcium excretion is decreased by diuretics pharmacologically related to indapamide. After 6 to 8 weeks of indapamide 1.25 mg treatment and in long-term studies of hypertensive patients with higher doses of indapamide, however, serum concentrations of calcium increased only slightly with indapamide. Prolonged treatment with drugs pharmacologically related to indapamide may in rare instances be associated with hypercalcemia and hypophosphatemia secondary to physiologic changes in the parathyroid gland; however, the common complications of hyperparathyroidism, such as renal lithiasis, bone resorption, and peptic ulcer, have not been seen. Treatment should be discontinued before tests for parathyroid function are performed. Like the thiazides, indapamide may decrease serum PBI levels without signs of thyroid disturbance.

Interaction with Systemic Lupus Erythematosus

Thiazides have exacerbated or activated systemic lupus erythematosus and this possibility should be considered with indapamide as well.

Acute Angle-Closure Glaucoma, Acute Myopia, and Choroidal Effusion

Sulfonamide or sulfonamide-derivative drugs, like indapamide, can cause an idiosyncratic reaction resulting in acute angle-closure glaucoma and elevated intraocular pressure with or without a noticeable acute myopic shift and/or choroidal effusions. Symptoms may include acute onset of decreased visual acuity or ocular pain and typically occur within hours to weeks of drug initiation. Untreated, the angle-closure glaucoma may result in permanent visual field loss. The primary treatment is to discontinue indapamide as rapidly as possible. Prompt medical or surgical treatments may need to be considered if the intraocular pressure remains uncontrolled. Risk factors for developing acute angle-closure glaucoma may include a history of sulfonamide or penicillin allergy.

Drug Interactions

Other Antihypertensives

Indapamide may add to or potentiate the action of other antihypertensive drugs. In limited controlled trials that compared the effect of indapamide combined with other antihypertensive drugs with the effect of the other drugs administered alone, there was no notable change in the nature or frequency of adverse reactions associated with the combined therapy.

Lithium

See WARNINGS.

Post-Sympathectomy Patient

The antihypertensive effect of the drug may be enhanced in the post-sympathectomized patient.

Norepinephrine

Indapamide, like the thiazides, may decrease arterial responsiveness to norepinephrine, but this diminution is not sufficient to preclude effectiveness of the pressor agent for therapeutic use.

Carcinogenesis, Mutagenesis, Impairment of Fertility

Both mouse and rat lifetime carcinogenicity studies were conducted. There was no significant difference in the incidence of tumors between the indapamide-treated animals and the control groups.

Pregnancy

Teratogenic Effects

Reproduction studies have been performed in rats, mice and rabbits at doses up to 6,250 times the therapeutic human dose and have revealed no evidence of impaired fertility or harm to the fetus due to indapamide. Postnatal development in rats and mice was unaffected by pretreatment of parent animals during gestation. There are, however, no adequate and well controlled studies in pregnant women. Moreover, diuretics are known to cross the placental barrier and appear in cord blood. Because animal reproduction studies are not always predictive of human response, this drug should be used during pregnancy only if clearly needed. There may be hazards associated with this use such as fetal or neonatal jaundice, thrombocytopenia, and possibly other adverse reactions that have occurred in the adult.

Nursing Mothers

It is not known whether this drug is excreted in human milk. Because most drugs are excreted in human milk, if use of this drug is deemed essential, the patient should stop nursing.

Pediatric Use

Safety and effectiveness of indapamide in pediatric patients have not been established.

Geriatric Use

Clinical studies of indapamide did not include sufficient numbers of subjects aged 65 and over to determine whether they respond differently from younger subjects. Other reported clinical experience has not identified differences in responses between the elderly and younger patients. In general, dose selection for an elderly patient should be cautious, usually starting at the low end of the dosing range, reflecting the greater frequency of decreased hepatic, renal, or cardiac function, and of concomitant disease or other drug therapy.

Severe cases of hyponatremia, accompanied by hypokalemia have been reported with recommended doses of indapamide in elderly females (see WARNINGS).

ADVERSE REACTIONS

Most adverse effects have been mild and transient.

The clinical adverse reactions listed in Table 1 represent data from Phase II/III placebo-controlled studies (306 patients given indapamide 1.25 mg). The clinical adverse reactions listed in Table 2 represent data from Phase II placebo-controlled studies and long-term controlled clinical trials (426 patients given indapamide 2.5 mg or 5 mg). The reactions are arranged into two groups: 1) a cumulative incidence equal to or greater than 5%; 2) a cumulative incidence less than 5%. Reactions are counted regardless of relation to drug.

TABLE 1: Adverse Reactions from Studies of 1.25 mg
Incidence ≥ 5% | Incidence < 5%^1
BODY AS A WHOLE
Headache Infection Pain Back Pain | Asthenia Flu Syndrome Abdominal Pain Chest Pain
GASTROINTESTINAL SYSTEM
 | Constipation Diarrhea Dyspepsia Nausea
METABOLIC SYSTEM
 | Peripheral Edema
CENTRAL NERVOUS SYSTEM
Dizziness | Nervousness Hypertonia
RESPIRATORY SYSTEM
Rhinitis | Cough Pharyngitis Sinusitis
SPECIAL SENSES
 | Conjunctivitis
^1OTHER
All other clinical adverse reactions occurred at an incidence of < 1%.

Approximately 4% of patients given indapamide 1.25 mg compared to 5% of the patients given placebo discontinued treatment in the trials of up to 8 weeks because of adverse reactions.

In controlled clinical trials of 6 to 8 weeks in duration, 20% of patients receiving indapamide 1.25 mg, 61% of patients receiving indapamide 5 mg, and 80% of patients receiving indapamide 10 mg had at least one potassium value below 3.4 mEq/L. In the indapamide 1.25 mg group, about 40% of those patients who reported hypokalemia as a laboratory adverse event returned to normal serum potassium values without intervention. Hypokalemia with concomitant clinical signs or symptoms occurred in 2% of patients receiving indapamide 1.25 mg.

TABLE 2: Adverse Reactions from Studies of 2.5 mg and 5 mg
Incidence ≥ 5% | Incidence < 5%
CENTRAL NERVOUS SYSTEM/NEUROMUSCULAR
Headache Dizziness Fatigue, weakness, loss of energy, lethargy, tiredness, or malaise Muscle cramps or spasm, or numbness of the extremities Nervousness, tension, anxiety, irritability, or agitation | Lightheadedness Drowsiness Vertigo Insomnia Depression Blurred Vision
GASTROINTESTINAL SYSTEM
 | Constipation Nausea Vomiting Diarrhea Gastric irritation Abdominal pain or cramps Anorexia
CARDIOVASCULAR SYSTEM
 | Orthostatic hypotension Premature ventricular contractions Irregular heart beat Palpitations
GENITOURINARY SYSTEM
 | Frequency of urination Nocturia Polyuria
DERMATOLOGIC/HYPERSENSITIVITY
 | Rash Hives Pruritus Vasculitis
OTHER
 | Impotence or reduced libido Rhinorrhea Flushing Hyperuricemia Hyperglycemia Hyponatremia Hypochloremia Increase in serum urea nitrogen (BUN) or creatinine Glycosuria Weight loss Dry mouth Tingling of extremities

Because most of these data are from long-term studies (up to 40 weeks of treatment), it is probable that many of the adverse experiences reported are due to causes other than the drug. Approximately 10% of patients given indapamide discontinued treatment in long-term trials because of reactions either related or unrelated to the drug.

Hypokalemia with concomitant clinical signs or symptoms occurred in 3% of patients receiving indapamide 2.5 mg q.d. and 7% of patients receiving indapamide 5 mg q.d. In long-term controlled clinical trials comparing the hypokalemic effects of daily doses of indapamide and hydrochlorothiazide, however, 47% of patients receiving indapamide 2.5 mg, 72% of patients receiving indapamide 5 mg, and 44% of patients receiving hydrochlorothiazide 50 mg had at least one potassium value (out of a total of 11 taken during the study) below 3.5 mEq/L. In the indapamide 2.5 mg group, over 50% of those patients returned to normal serum potassium values without intervention.

In clinical trials of 6 to 8 weeks, the mean changes in selected values were as shown in the tables below.

Mean Changes from Baseline after 8 Weeks of Treatment - 1.25 mg
 | Serum Electrolytes (mEq/L) |  |  | Serum Uric Acid (mg/dL) | BUN (mg/dL)
 | Potassium | Sodium | Chloride | Serum Uric Acid (mg/dL) | BUN (mg/dL)
Indapamide 1.25 mg (n=255 to 257) | -0.28 | -0.63 | -2.60 | 0.69 | 1.46
Placebo (n=263 to 266) | 0.00 | -0.11 | -0.21 | 0.06 | 0.06

No patients receiving indapamide 1.25 mg experienced hyponatremia considered possibly clinically significant (< 125 mEq/L).

Indapamide had no adverse effects on lipids.

Mean Changes from Baseline after 40 Weeks of Treatment - 2.5 mg and 5 mg
 | Serum Electrolytes (mEq/L) |  |  | Serum Uric Acid (mg/dL) | BUN (mg/dL)
 | Potassium | Sodium | Chloride | Serum Uric Acid (mg/dL) | BUN (mg/dL)
Indapamide 2.5 mg (n=76) | -0.4 | -0.6 | -3.6 | 0.7 | -0.1
Indapamide 5 mg (n=81) | -0.6 | -0.7 | -5.1 | 1.1 | 1.4

The following reactions have been reported with clinical usage of indapamide: jaundice (intrahepatic cholestatic jaundice), hepatitis, pancreatitis, and abnormal liver function tests. These reactions were reversible with discontinuance of the drug.

Also reported are erythema multiforme, Stevens-Johnson Syndrome, bullous eruptions, purpura, photosensitivity, fever, pneumonitis, anaphylactic reactions, agranulocytosis, leukopenia, thrombocytopenia, and aplastic anemia. Other adverse reactions reported with antihypertensive/diuretics are necrotizing angiitis, respiratory distress, sialadenitis, xanthopsia.

Postmarketing Experience

Eye Disorders

Choroidal effusion, acute myopia, and angle-closure glaucoma (frequency not known).^1

^1Module 2.5 SER-indapamide-choroidal effusion-acute myopia and angle-closure glaucoma-Jul2020.

OVERDOSAGE

Symptoms of overdosage include nausea, vomiting, weakness, gastrointestinal disorders, and disturbances of electrolyte balance. In severe instances, hypotension and depressed respiration may be observed. If this occurs, support of respiration and cardiac circulation should be instituted. There is no specific antidote. An evacuation of the stomach is recommended by emesis and gastric lavage after which the electrolyte and fluid balance should be evaluated carefully.

DOSAGE AND ADMINISTRATION

Hypertension

The adult starting indapamide dose for hypertension is 1.25 mg as a single daily dose taken in the morning. If the response to 1.25 mg is not satisfactory after 4 weeks, the daily dose may be increased to 2.5 mg taken once daily. If the response to 2.5 mg is not satisfactory after 4 weeks, the daily dose may be increased to 5 mg taken once daily, but adding another antihypertensive should be considered.

Edema of Congestive Heart Failure

The adult starting indapamide dose for edema of congestive heart failure is 2.5 mg as a single daily dose taken in the morning. If the response to 2.5 mg is not satisfactory after one week, the daily dose may be increased to 5 mg taken once daily.

If the antihypertensive response to indapamide is insufficient, indapamide may be combined with other antihypertensive drugs, with careful monitoring of blood pressure. It is recommended that the usual dose of other agents be reduced by 50% during initial combination therapy. As the blood pressure response becomes evident, further dosage adjustments may be necessary.

In general, doses of 5 mg and larger have not appeared to provide additional effects on blood pressure or heart failure, but are associated with a greater degree of hypokalemia. There is minimal clinical trial experience in patients with doses greater than 5 mg once a day.

HOW SUPPLIED

Indapamide Tablets USP

The 2.5 mg tablets are white, round, film coated tablets debossed ‘ANI’ over ‘511’ on one side and plain on the other side.

- NDC 72162-1767-1: 100 Tablets in a BOTTLE

Store at 20° to 25°C (68° to 77°F) [see USP Controlled Room Temperature].

Keep container tightly closed.

Avoid excessive heat.

Dispense in a tight, light-resistant container as defined in the USP using a child-resistant closure.

Repackaged/Relabeled by:
Bryant Ranch Prepack
Burbank, CA 91504

PACKAGE LABEL

Indapamide 2.5mg Tablets